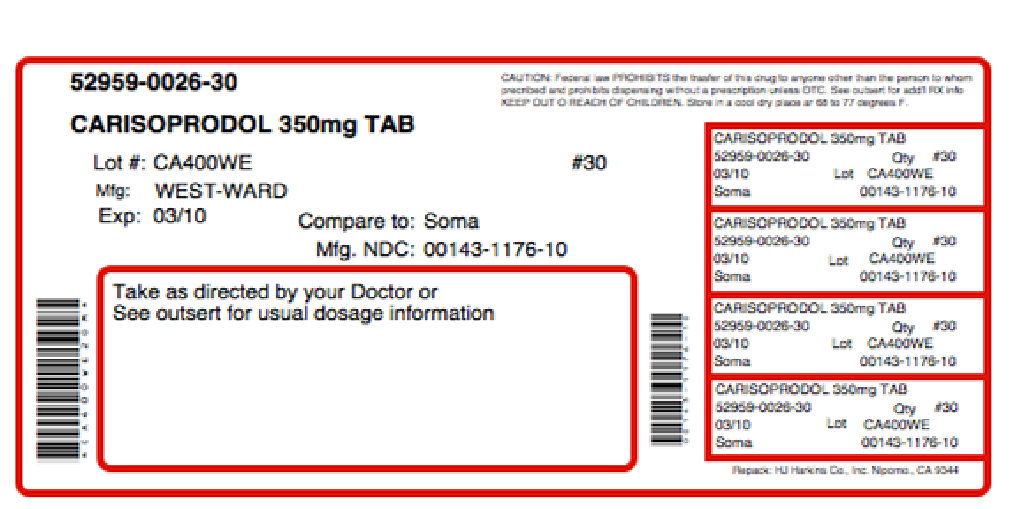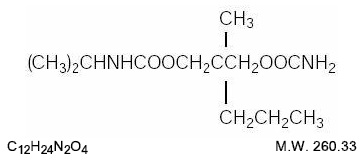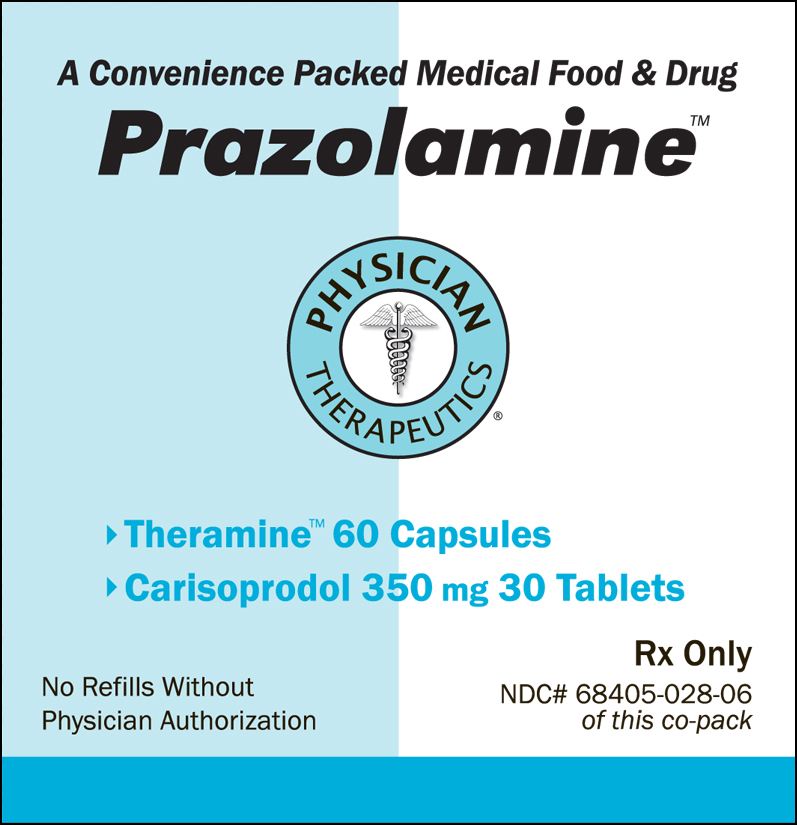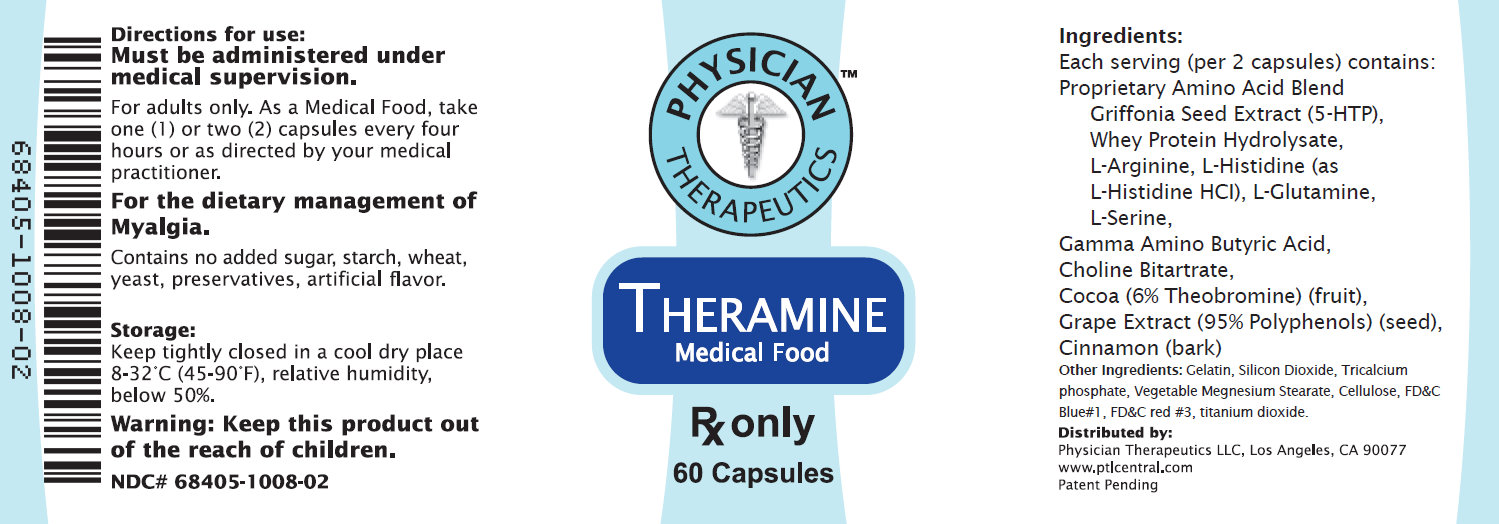 DRUG LABEL: Prazolamine
NDC: 68405-028 | Form: KIT | Route: ORAL
Manufacturer: Physician Therapeutics LLC
Category: prescription | Type: HUMAN PRESCRIPTION DRUG LABEL
Date: 20110801

ACTIVE INGREDIENTS: CARISOPRODOL 350 mg/1 1; .GAMMA.-AMINOBUTYRIC ACID 100 mg/1 1
INACTIVE INGREDIENTS: LACTOSE MONOHYDRATE; MAGNESIUM STEARATE; CELLULOSE, MICROCRYSTALLINE; POVIDONE; STARCH, CORN; SODIUM LAURYL SULFATE; SODIUM STARCH GLYCOLATE TYPE A POTATO; SILICON DIOXIDE; STEARIC ACID; MAGNESIUM STEARATE; CELLULOSE, MICROCRYSTALLINE; MALTODEXTRIN; GELATIN

HIGHLIGHTS OF PRESCRIBING INFORMATION

Carisoprodol Tablets, USP Rx only Rev. 09/09 These highlights do not include all the information needed to use Carisoprodol Tablets safely and effectively. See full prescribing information for Carisoprodol Tablets. Initial U.S. Approval Carisoprodol Tablets for Oral use

RECENT MAJOR CHANGES

Indications and Usage (1) 9/2007
Dosage and Administration (2) 9/2007

INDICATIONS AND USAGE

Carisoprodol Tablets are indicated for the relief of discomfort associated
with acute, painful musculoskeletal conditions. (1)
Important Limitations:
• Should only be used for acute treatment periods up to two or three
weeks (1)
• Not recommended in pediatric patients less than 16 years of age (8.4)

DOSAGE AND ADMINISTRATION

• Recommended dose is 350 mg three times a day and at bedtime. (2)

DOSAGE FORMS AND STRENGTHS

Tablets: 350 mg (3)

CONTRAINDICATIONS

• Acute intermittent porphyria (4)
• Hypersensitivity reactions to a carbamate such as meprobamate (4)

WARNINGS AND PRECAUTIONS

• Due to sedative properties, may impair ability to perform hazardous
tasks such as driving or operating machinery (5.1)
• Additive sedative effects when used with other CNS depressants including
alcohol (5.1)
• Cases of Drug Dependence, Withdrawal, and Abuse (5.2)
• Seizures (5.3)

ADVERSE REACTIONS

Most common adverse reactions (incidence > 2%) are drowsiness,
dizziness, and headache (6.1)
To report SUSPECTED ADVERSE REACTIONS, contact West-ward
Pharmaceutical Corp. at 1-877-233-2001 or FDA at 1-800-FDA-1088 or
www.fda.gov/medwatch.

DRUG INTERACTIONS

• CNS depressants (e.g., alcohol, benzodiazepines, opioids, tricyclic
antidepressants) – additive sedative effects (5.1 and 7.1)

FULL PRESCRIBING INFORMATION

1 INDICATIONS AND USAGE

Carisoprodol Tablets are indicated for the relief of discomfort associated with acute, painful musculoskeletal conditions in adults.
Carisoprodol Tablets should only be used for short periods (up to two or three weeks) because adequate evidence of effectiveness for more
prolonged use has not been established and because acute, painful musculoskeletal conditions are generally of short duration. [see Dosage and Administration (2)].

2 DOSAGE AND ADMINISTRATION

The recommended dose of Carisoprodol Tablets is 350 mg three times a day and at bedtime. The recommended maximum duration of Carisoprodol Tablets use is up to two or three weeks.

3 DOSAGE FORMS AND STRENGTHS

Carisoprodol Tablets, USP 350 mg are white, round, unscored tablets; imprinted “WW 176”.

4 CONTRAINDICATIONS

Carisoprodol Tablets are contraindicated in patients with a history of acute intermittent porphyria or a hypersensitivity reaction to a carbamate such as meprobamate.

5 WARNINGS AND PRECAUTIONS 5.1 Sedation 5.2 Drug Dependence, Withdrawal, and Abuse 5.3 Seizures

5 WARNINGS AND PRECAUTIONS
5.1 Sedation
Carisoprodol Tablets may have sedative properties (in the low back pain trials, 13% to 17% of patients who received Carisoprodol Tablets experienced sedation compared to 6% of patients who received placebo) [see ADVERSE REACTIONS (6.1)] and may impair the mental and/or physical abilities required for the performance of potentially hazardous tasks such as driving a motor vehicle or operating machinery. Since the sedative effects of Carisoprodol Tablets and other CNS depressants (e.g., alcohol, benzodiazepines, opioids, tricyclic antidepressants) may be additive, appropriate caution should be exercised with patients who take more than one of these CNS depressants simultaneously.

5.2 Drug Dependence, Withdrawal, and Abuse In the postmarketing experience with Carisoprodol Tablets, cases of dependence, withdrawal, and abuse have been reported with prolonged use. Most cases of dependence withdrawal, and abuse occurred in patients
who have had a history of addiction or who used Carisoprodol Tablets in combination with other drugs with abuse potential. Withdrawal symptoms have been reported following abrupt cessation after prolonged use. To reduce the chance of Carisoprodol Tablets dependence, withdrawal, or abuse, Carisoprodol Tablets should be used with caution in addiction prone patients and in patients taking other CNS depressants including alcohol, and Carisoprodol Tablets should not be used more than two to three weeks for the relief of acute musculoskeletal discomfort. One of the metabolites of Carisoprodol Tablets, meprobamate (a controlled substance), may cause dependence. [see Clinical Pharmacology (12.3)].

5.3 Seizures
There have been postmarketing reports of seizures in patients who received Carisoprodol Tablets. Most of these cases have occurred in the setting of multiple drug overdoses (including drugs of abuse, illegal drugs, and alcohol) [see Overdosage (10)].

6 ADVERSE REACTIONS 6.1 Clinical Studies Experience 6.2 Post-marketing Experience

6 ADVERSE REACTIONS
6.1 Clinical Studies Experience
Because clinical studies are conducted under widely varying conditions, adverse reaction rates observed in clinical studies of a drug cannot be directly compared to rates in the clinical studies of another drug and may not reflect rates observed in practice. The data described below are based on 1387 patients pooled from two double blind, randomized, multicenter, placebo controlled, one-week trials in adult patients with acute, mechanical, lower back pain [see Clinical Studies (14)]. In the study, patients were treated with 350 mg of Carisoprodol Tablets, or placebo three times a day and at bedtime for seven days. The mean age was about 41 years old with 54% females and 46% males and 74% Caucasian, 16% Black, 9% Asian, and 2% other. There were no deaths and there were no serious adverse reactions in the trial. In the study, 2.7% and 5.4% of patients treated with placebo and 350 mg of Carisoprodol Tablets, respectively, discontinued due to adverse events; and 0.5% and 1.8% of patients treated with placebo and 350 mg of Carisoprodol Tablets, respectively, discontinued due to central nervous system adverse reactions.

Table 1 displays adverse reactions reported with frequencies greater than 2% and more frequently than placebo in patients treated with Carisoprodol Tablets in the trial described above.

Table 1. Patients with Adverse Reactions in Controlled Study
Adverse Reaction | Placebo (n=560) n (%) | Carisoprodol Tablets 350 mg (n=279) n (%)
Drowsiness | 31 (6) | 47 (17)
Dizziness | 11 (2) | 47 (17)
Headache | 11 (2) | 9 (3)

6.2 Postmarketing Experience
The following events have been reported during postapproval use of Carisoprodol Tablets. Because these reactions are reported voluntarily from a population of uncertain size, it is not always possible to reliably estimate their frequency or establish a causal relationship to drug exposure. Cardiovascular: Tachycardia, postural hypotension, and facial flushing [see Overdosage (10)]. Central Nervous System: Drowsiness, dizziness, vertigo, ataxia, tremor, agitation, irritability, headache, depressive reactions, syncope, insomnia,
and seizures [see Overdosage (10)]. Gastrointestinal: Nausea, vomiting, and epigastric discomfort. Hematologic: Leukopenia, pancytopenia.

7 DRUG INTERACTIONS 7.1 CNS Depressants 7.2 CYP2C19 Inhibitors and Inducers

7 DRUG INTERACTIONS

7.1 CNS Depressants
The sedative effects of Carisoprodol Tablets and other CNS depressants (e.g., alcohol, benzodiazepines, opioids, tricyclic antidepressants) may be additive. Therefore, caution should be exercised with patients who take more than one of these CNS depressants simultaneously. Concomitant use of Carisoprodol Tablets and meprobamate, a metabolite of Carisoprodol Tablets, is not recommended [see Warnings and Precautions (5.1)].

7.2 CYP2C19 Inhibitors and Inducers Carisoprodol Tablets are metabolized in the liver by CYP2C19 to form meprobamate [see Clinical Pharmacology (12.3)]. Co-administration of CYP2C19 inhibitors, such as omeprazole or fluvoxamine, with Carisoprodol Tablets could result in increased exposure of carisoprodol and decreased exposure of meprobamate. Co-administration of CYP2C19 inducers,such as rifampin or St. John’s Wort, with Carisoprodol Tablets could result in decreased exposure of carisoprodol and increased exposure of meprobamate. Low dose aspirin also showed induction effect on CYP2C19.
The full pharmacological impact of these potential alterations of exposures in terms of either efficacy or safety of Carisoprodol Tablets is unknown.

8 USE IN SPECIFIC POPULATIONS 8.1 Pregnancy: Pregnancy Category C.

8.1 Pregnancy: Category Pregnancy C.
There are no data on the use of Carisoprodol Tablets during human pregnancy. Animal studies indicate that carisoprodol crosses the placenta and results in adverse effects on fetal growth and postnatal survival. The primary metabolite of carisoprodol, meprobamate, is an approved anxiolytic. Retrospective, post-marketing studies do not show a consistent association between maternal use of meprobamate and an increased risk for particular congenital malformations. Teratogenic effects: Animal studies have not adequately evaluated the teratogenic effects of carisoprodol. There was no increase in the incidence of congenital malformations noted in reproductive studies in rats, rabbits, and mice treated with meprobamate. Retrospective, post-marketing studies of meprobamate during human pregnancy were equivocal for demonstrating an increased risk of congenital malformations following first trimester exposure. Across studies that indicated an increased risk, the types of malformations were inconsistent. Nonteratogenic effects: In animal studies, carisoprodol reduced fetal weights, postnatal weight gain, and postnatal survival at maternal doses equivalent to 1-1.5 times the human dose (based on a body surface area comparison). Rats exposed to meprobamate in utero showed behavioral alterations that persisted into adulthood. For children exposed to meprobamate in utero, one study found no adverse effects on mental or motor development or IQ scores. Carisoprodol Tablets should be used during pregnancy only if the potential benefit justifies the risk to the fetus.

8.2 Labor and Delivery

There is no information about the effects of Carisoprodol Tablets on the mother and the fetus during labor and delivery.

8.3 Nursing Mothers

Very limited data in humans show that Carisoprodol Tablets is present in breast milk and may reach concentrations two to four times the maternal plasma concentrations. In one case report, a breast-fed infant received about 4-6% of the maternal daily dose through breast milk and experienced no adverse effects. However, milk production was inadequate and the baby was supplemented with formula. In lactation studies in mice, female pup survival and pup weight at weaning were decreased. This information suggests that maternal use of Carisoprodol Tablets may lead to reduced or less effective infant feeding (due to sedation) and/or decreased milk production. Caution should be exercised when Carisoprodol Tablets are administered to a nursing woman

8.4 Pediatric Use

The efficacy, safety, and pharmacokinetics of Carisoprodol Tablets in pediatric patients less than 16 years of age have not been established.

8.5 Geriatric Use

The efficacy, safety, and pharmacokinetics of Carisoprodol Tablets in patients over 65 years old have not been established.

8.6 Renal Impairment 8.7 Hepatic Impairment 8.8 Patients with Reduced CYP2C19 Activity

8.6 Renal Impairment
The safety and pharmacokinetics of Carisoprodol Tablets in patients with renal impairment have not been evaluated. Since Carisoprodol Tablets are excreted by the kidney, caution should be exercised if Carisoprodol Tablets are administered to patients with impaired renal function. Carisoprodol Tablets are dialyzable by hemodialysis and peritoneal dialysis.

8.7 Hepatic Impairment
The safety and pharmacokinetics of Carisoprodol Tablets in patients with hepatic impairment have not been evaluated. Since Carisoprodol Tablets are metabolized in the liver, caution should be exercised if Carisoprodol Tablets are administered to patients with impaired hepatic function.

8.8 Patients with Reduced CYP2C19 Activity
Patients with reduced CYP2C19 activity have higher exposure to Carisoprodol Tablets. Therefore, caution should be exercised in administration of Carisoprodol Tablets to these patients. [see Clinical Pharmacology (12.3)].

9 DRUG ABUSE AND DEPENDENCE

[see Warnings and Precautions (5.2)]

5.2 Drug Dependence, Withdrawal, and Abuse
In the postmarketing experience with Carisoprodol Tablets, cases of dependence, withdrawal, and abuse have been reported with prolonged use. Most cases of dependence withdrawal, and abuse occurred in patients who have had a history of addiction or who used Carisoprodol Tablets in combination with other drugs with abuse potential. Withdrawal symptoms have been reported following abrupt cessation after prolonged use. To reduce the chance of Carisoprodol Tablets dependence, withdrawal, or abuse, Carisoprodol Tablets should be used with caution in addictionprone patients and in patients taking other CNS depressants including alcohol, and Carisoprodol Tablets should not be used more than two to three weeks for the relief of acute musculoskeletal discomfort.
One of the metabolites of Carisoprodol Tablets, meprobamate (a controlled substance), may cause dependence. [see Clinical Pharmacology (12.3)].

10 OVERDOSAGE

Overdosage of Carisoprodol Tablets commonly produces CNS depression. Death, coma, respiratory depression, hypotension, seizures, delirium, hallucinations, dystonic reactions, nystagmus, blurred vision, mydriasis, euphoria, muscular incoordination, rigidity, and/or headache have been reported with Carisoprodol Tablets overdosage. Many of the Carisoprodol Tablets over-doses have occurred in the setting of multiple drug overdoses (including drugs of abuse, illegal drugs, and alcohol). The effects of an overdose of Carisoprodol Tablets and other CNS depressants (e.g., alcohol, benzodiazepines, opioids, tricyclic antidepressants) can be additive even when one of the drugs has been taken in the recommended dosage. Fatal accidental and non-accidental overdoses of Carisoprodol Tablets have been reported alone or in combination with CNS depressants.

Treatment of Overdosage: Basic life support measures should be instituted as dictated by the clinical presentation of Carisoprodol Tablets overdose. Induced emesis is not recommended due to the risk of CNS and respiratory depression, which may increase the risk of aspiration pneumonia. Gastric lavage should be considered soon after ingestion (within one hour). Circulatory support should be administered with volume infusion and vasopressor agents if needed. Seizures should be treated with intravenous benzodiazepines and the reoccurrence of seizures may be treated with phenobarbital. In cases of severe CNS depression, airway protective reflexes may be compromised and tracheal intubation should be considered for airway protection and respiratory support. The following types of treatment have been used successfully with an overdose of meprobamate, a metabolite of carisoprodol: activated charcoal (oral or via nasogastric tube), forced diuresis, peritoneal dialysis, and hemodialysis (carisoprodol is also dialyzable). Careful monitoring of urinary output is necessary and overhydration should be avoided. Observe for possible relapse due to incomplete gastric emptying and delayed absorption. For more information on the management of an overdose of Carisoprodol Tablets, contact a Poison Control Center.

11 DESCRIPTION

Carisoprodol Tablets, USP are available as 350 mg round, white tablets. Carisoprodol is a white, crystalline powder, having a mild, characteristic odor and a bitter taste. It is slightly soluble in water; freely soluble in alcohol, in chloroform, and in acetone; and its solubility is practically independent of pH. Carisoprodol is present as a racemic mixture. Chemically, carisoprodol is N-isopropyl-2-methyl-2-propyl-1,3- propanediol dicarbamate and the molecular formula is C12H24N2O4 , with a molecular weight of 260.33. The structural formula is:

Other Ingredients: colloidal silicon dioxide, lactose monohydrate, magnesium stearate, microcrystalline cellulose, methylcellulose, povidone, sodium lauryl sulphate, sodium starch glycolate, and stearic acid.

12 CLINCIAL PHARMACOLOGY 12.1 Mechanism of Action

12 CLINICAL PHARMACOLOGY
12.1 Mechanism of Action
The mechanism of action of carisoprodol in relieving discomfort associated with acute painful musculoskeletal conditions has not been clearly identified.
In animal studies, muscle relaxation induced by carisoprodol is associated with altered interneuronal activity in the spinal cord and in the descending reticular formation of the brain.

12.2 Pharmacodynamics

Carisoprodol is a centrally acting skeletal muscle relaxant that does not directly relax skeletal muscles. A metabolite of carisoprodol, meprobamate, has anxiolytic and sedative properties. The degree to which these properties of meprobamate contribute to the safety and efficacy of Carisoprodol Tablets is unkown.

12.3 Pharmacokinetics

The pharmacokinetics of carisoprodol and its metabolite meprobamate were studied in a crossover study of 24 healthy subjects (12 male and 12 female) who received single doses 350 mg carisoprodol (see Table 2). The Cmax of meprobamate was 2.5 ± 0.5 μg/mL (mean ± SD) after administration of a single 350 mg dose of carisoprodol, which is approximately 30% of the Cmax of meprobamate (approximately 8 μg/mL) after administration of a single 400 mg dose of meprobamate.

Table 2. Pharmacokinetic Parameters of Carisoprodol and Meprobamate (Mean ± SD, n=24)
 | Carisoprodol 350 mg
Carisoprodol | Carisoprodol
Cmax (μg/mL) | 1.8 ± 1.0
AUCinf (μg*hr/mL) | 7.0 ± 5.0
Tmax (hr) | 1.7 ± 0.8
T1/2 (hr) | 2.0 ± 0.5
Meprobamate | Meprobamate
Cmax (μg/mL) | 2.5 ± 0.5
AUCinf (μg*hr/mL) | 46 ± 9.0
Tmax (hr) | 4.5 ± 1.9
T1/2 (hr) | 9.6 ± 1.5

Absorption: Absolute bioavailability of carisoprodol has not been determined. The mean time to peak plasma concentrations (Tmax) of carisoprodol was approximately 1.5 to 2 hours. Co-administration of a high-fat meal with carisoprodol (350 mg tablet) had no effect on the pharmacokinetics of carisoprodol. Therefore, Carisoprodol Tablets may be administered with or without food.

Metabolism: The major pathway of carisoprodol metabolism is via the liver by cytochrome enzyme CYP2C19 to form meprobamate. This enzyme exhibits genetic polymorphism (see Patients with Reduced CYP2C19 Activity below).

Elimination: Carisoprodol is eliminated by both renal and non-renal routes with a terminal elimination half-life of approximately 2 hours. The half-life of meprobamate is approximately 10 hours.

Gender: Exposure of carisoprodol is higher in female than in male subjects (approximately 30-50% on a weight adjusted basis). Overall exposure of meprobamate is comparable between female and male subjects. Patients with Reduced CYP2C19 Activity: Carisoprodol Tablets should be used with caution in patients with reduced CYP2C19 activity. Published studies indicate that patients who are poor CYP2C19 metabolizers have a 4-fold increase in exposure to carisoprodol, and concomitant 50% reduced exposure to meprobamate compared to normal CYP2C19 metabolizers. The prevalence of poor metabolizers in Caucasians and African Americans is approximately 3-5% and in Asians is approximately 15-20%.

13 NONCLINICAL TOXICOLOGY 13.1 Carcinogenesis, Mutagenesis, Impairment of Fertility

13 NONCLINICAL TOXICOLOGY
13.1 Carcinogenesis, Mutagenesis, Impairment of Fertility
Long term studies in animals have not been performed to evaluate the carcinogenic potential of carisoprodol. Carisoprodol Tablets were not formally evaluated for genotoxicity. In published studies, carisoprodol was mutagenic in the in vitro mouse lymphoma cell assay in the absence of metabolizing enzymes, but was not mutagenic in the presence of metabolizing enzymes. Carisoprodol was clastogenic in the in vitro chromosomal aberration assay using Chinese hamster ovary cells with or without the presence of metabolizing enzymes.
Other types of genotoxic tests resulted in negative findings. Carisoprodol was not mutagenic in the Ames reverse mutation assay using S. typhimurium strains with or without metabolizing enzymes, and was not clastogenic in an in vivo mouse micronucleus assay of circulating blood cells. Carisoprodol Tablets were not formally evaluated for effects on fertility. Published reproductive studies of carisoprodol in mice found no alteration in fertility although an alteration in reproductive cycles characterized by a greater time spent in estrus was observed at a carisoprodol dose of 1200 mg/kg/day. In a 13-week toxicology study that did not determine fertility, mouse testes weight and sperm motility were reduced at a dose of 1200 mg/kg/day. In both studies, the no effect level was 750 mg/kg/day, corresponding to approximately 2.6 times the human equivalent dosage of 350 mg four times a day, based on a body surface area comparison. The significance of these findings for human fertility is not known.

14 CLINICAL STUDIES

The safety and efficacy of Carisoprodol Tablets for the relief of acute, idiopathic mechanical low back pain was evaluated in one, 7-day, double blind, randomized, multicenter, placebo controlled, U.S. trial (Study 1). Patients had to be 18 to 65 years old and had to have acute back pain (≤ 3 days of duration) to be included in the trials. Patients with chronic back pain; at increased risk for vertebral fracture (e.g., history of osteoporosis); with a history of spinal pathology (e.g., herniated nucleus pulposis, spondylolisthesis or spinal stenosis); with inflammatory back pain, or with evidence of a neurologic deficit were excluded from participation. Concomitant use of analgesics (e.g., acetaminophen, NSAIDs, tramadol, opioid agonists), other muscle relaxants, botulinum toxin, sedatives (e.g., barbiturates, benzodiazepines, promethazine hydrochloride), and anti-epileptic drugs was prohibited.

In Study 1, patients were randomized to one of two treatment groups (i.e., carisoprodol 350 mg or placebo). In the study, patients received study medication three times a day and at bedtime for seven days. The primary endpoints were the relief from starting backache and the global impression of change, as reported by patients, on Study Day #3. Both endpoints were scored on a 5-point rating scale from 0 (worst outcome) to 4 (best outcome) in the study. The proportion of patients who used concomitant acetaminophen, NSAIDs,
tramadol, opioid agonists, other muscle relaxants, and benzodiazepines was similar in the treatment groups. The results for the primary efficacy evaluations in the acute, low back pain study are presented in Table 3.

Table 3. Results of the Primary Efficacy Endpointsa in Study 1
Study | Parameter | Placebo | Carisoprodol Tablets 350 mg
1 | Number of Patients | n=269 | n=273
1 | Relief from Starting Backache, Mean (SE)b | 1.4(0.1) | 1.8(0.1)
1 | Difference between Carisoprodol Tablets and Placebo, Mean (SE)b (95% Cl) |  | 0.4 (0.2, 0.6)
1 | Global Impression of Change, Mean (SE)b | 1.9(0.1) | 2.2(0.1)
1 | Difference between Carisoprodol Tablets and Placebo, Mean (SE)b (95% Cl) |  | 0.3 (0.1, 0.4)

a The primary efficacy endpoints (Relief from Starting Backache and Global Impression of Change) were assessed by the patients on Study Day #3. These endpoints were scored on a 5-point rating scale from 0 (worst outcome) to 4 (best outcome).
b Mean is the least squared mean and SE is the standard error of the mean.
Patients treated with Carisoprodol Tablets experienced improvement in function as measured by the Roland-Morris Disability Questionnaire (RMDQ) score on Days 3 and 7.

16 HOW SUPPLIED/STORAGE AND HANDLING

Carisoprodol Tablets, USP 350 mg, are white, round, unscored tablets; imprinted “WW 176”, are available in:

Bottles of 100 tablets
Bottles of 500 tablets
Bottles of 1000 tablets

Storage:
Store at 20°-25°C (68°-77°F). [See USP Controlled Room Temperature.] Dispense in a tight, light-resistant container as defined in the USP using a child-resistant closure.

17 PATIENT COUNSELING INFORMATION 17.1 Sedation 17.2 Avoidance of Alcohol and Other CNS Depressants 17.3 Carisoprodol Should Only Be Used for Short-Term Treatment

17 PATIENT COUNSELING INFORMATION
Patients should be advised to contact their physician if they experience any adverse reactions to Carisoprodol Tablets.

17.1 Sedation
Since Carisoprodol Tablets may cause drowsiness and/or dizziness, patients should be advised to assess their individual response to Carisoprodol Tablets before engaging in potentially hazardous activities such as driving a motor vehicle or operating machinery [see Warnings and Precautions (5.1)].

17.2 Avoidance of Alcohol and Other CNS Depressants
Patients should be advised to avoid alcoholic beverages while taking Carisoprodol Tablets and to check with their doctor before taking other CNS depressants such as benzodiazepines, opioids, tricyclic antidepressants, sedating antihistamines, or other sedatives [see Warnings and Precautions (5.1)].

17.3 Carisoprodol Tablets Should Only Be Used for Short-Term Treatment
Patients should be advised that treatment with Carisoprodol Tablets should be limited to acute use (up to two or three weeks) for the relief of acute, musculoskeletal discomfort. If symptoms still persist, patients should contact their healthcare provider for further evaluation.

Manufactured for: West-ward Pharmaceutical Corp Eatontown, NJ 07724

Manufactured by: Shasun Chemical and Drugs Ltd. Pondicherry, India

PACKAGE LABEL

Carisoprodol 350mg

Packaged by Bryant Ranch North Hollywood CA 91605

Carisprodol 350 mg (CIV) Tablet

Compare To

Soma 350mg (CIV) Tablet

WEST WARD PHARMACEUTICAL CORP

#60 EXP 03/11

NDC 6362913083

LOT 10038

May Cause Drowsiness/No Alcohol

Keep all drugs out of reach of children

Theramine™ PRODUCT INFORMATION
Theramine (U.S. patent pending) capsules by oral administration. A specially formulated Medical Food product, consisting of a proprietary blend of amino acids and polyphenol ingredients in specific proportions, for the dietary management of the metabolic processes associated with pain disorders and inflammatory conditions. (PD) (IC). Must be administered under physician supervision.
Medical Foods
Medical Food products are often used in hospitals (e.g., for burn victims or kidney dialysis patients) and outside of a hospital setting under a physician’s care for the dietary management of diseases in patients with particular medical or metabolic needs due to their disease or condition. Congress defined "Medical Food" in the Orphan Drug Act and Amendments of 1988 as "a food which is formulated to be consumed or administered enterally [or orally] under the supervision of a physician and which is intended for the specific dietary management of a disease or condition for which distinctive nutritional requirements, based on recognized scientific principles, are established by medical evaluation." Medical Foods are complex formulated products, requiring sophisticated and exacting technology. Theramine has been developed, manufactured, and labeled in accordance with both the statutory and the FDA regulatory definition of a Medical Food. Theramine must be used while the patient is under the ongoing care of a physician.
PAIN DISORDERS (PD) INFLAMMATORY CONDITIONS (IC)
PD and IC as a Metabolic Deficiency Disease
A critical component of the definition of a Medical Food is the requirement for a distinctive nutritional deficiency. FDA scientists have proposed a physiologic definition of a distinctive nutritional deficiency as follows: “the dietary management of patients with specific diseases requires, in some instances, the ability to meet nutritional requirements that differ substantially from the needs of healthy persons. For example, in establishing the recommended dietary allowances for general, healthy population, the Food and Nutrition Board of the Institute of Medicine National Academy of Sciences, recognized that different or distinctive physiologic requirements may exist for certain persons with "special nutritional needs arising from metabolic disorders, chronic diseases, injuries, premature birth, other medical conditions and drug therapies. Thus, the distinctive nutritional needs associated with a disease reflects the total amount needed by a healthy person to support life or maintain homeostasis, adjusted for the distinctive changes in the nutritional needs of the patient as a result of the effects of the disease process on absorption, metabolism and excretion.” It was also proposed that in patients with certain disease states who respond to nutritional therapies, a physiologic deficiency of the nutrient is assumed to exist. For example, if a patient with pain disorders responds to a tryptophan formulation by decreasing perceived pain, a deficiency of tryptophan is assumed to exist. Patients with pain disorders and inflammatory conditions are known to have nutritional deficiencies of tryptophan, choline, arginine, GABA, flavonoids, and certain antioxidants. Patients with pain disorders and inflammatory conditions frequently exhibit reduced plasma levels of tryptophan and GABA and have been shown to respond to oral administration of GABA, arginine, tryptophan, or a 5-hydoxytryptophan formulation. Research has shown that tryptophan, arginine or GABA reduced diets result in a fall of circulating tryptophan, arginine, and/or GABA.
Patients with pain disorders frequently exhibit activation of the degradation pathways that increases the turnover of GABA, arginine and/or tryptophan leading to a reduced level of production of serotonin, GABA or nitric oxide for a given precursor blood level. Research has also shown that a genetic predisposition to accelerated degradation can lead to increased precursor requirements in certain patients with pain disorders and inflammatory conditions.
Choline is required to fully potentiate acetylcholine synthesis by brain neurons. A deficiency of choline leads to reduced acetylcholine production by the neurons. Flavonoids potentiate the production of acetylcholine by the neurons thereby reducing delta pain. Diets deficient in flavonoid rich foods and choline result in inadequate flavonoid concentrations, impeding acetylcholine production in certain patients with pain disorders and/or inflammatory conditions. Acetylcholine in pre-synaptic ganglia is necessary for the production of serotonin and nitric oxide in post-synaptic ganglia. Provision of tryptophan, arginine, GABA, choline and flavonoids with antioxidants, in specific proportions can restore the production of beneficial serotonin, nitric oxide, and acetylcholine, thereby reducing the perception of pain and reducing inflammation. L-Histidine is known to produce brain histamine that stimulates production of ACTH.

PRODUCT DESCRIPTION
Primary Ingredients Theramine consists of a proprietary blend of amino acids, cocoa, caffeine, cinnamon, and flavonoids in specific proportions. These ingredients fall into the category of Generally Regarded as Safe” (GRAS) as defined by the Food and Drug Administration (FDA) (Sections 201(s) and 409 of the Federal Food, Drug, and Cosmetic Act). A GRAS substance is distinguished from a food additive on the basis of the common knowledge about the safety of the substance for its intended use. The standard for an ingredient to achieve GRAS status requires not only technical demonstration of non-toxicity and safety, but also general recognition of safety through widespread usage and agreement of that safety by experts in the field. Many ingredients have been determined by the U.S. Food and Drug Administration (FDA) to be GRAS, and are listed as such by regulation, in Volume 21 Code of Federal Regulations (CFR) Sections 182, 184, and 186.
Amino Acids
Amino Acids are the building blocks of protein. All amino acids are GRAS listed as they have been ingested by humans for thousands of years. The doses of the amino acids in Theramine are equivalent to those found in the usual human diet. Patients with pain disorders may require an increased amount of certain amino acids that cannot be obtained from normal diet alone. Tryptophan, for example, is an obligatory amino acid. The body cannot make tryptophan and must obtain tryptophan from the diet. Tryptophan is needed to produce serotonin. Serotonin is required to reduce pain. Patients with pain disorders and inflammatory conditions have altered serotonin metabolism. Some patients with pain disorders and inflammatory conditions have a resistance to the use of tryptophan that is similar to the mechanism found in insulin resistance. Patients with pain disorders and inflammatory conditions cannot acquire sufficient tryptophan from the diet to alter the perception of pain and the inflammatory process without ingesting a prohibitively large amount of calories, particularly calories from protein.
Flavonoids
Flavonoids are a group of phytochemical compounds found in all vascular plants including fruits and vegetables. They are a part of a larger class of compounds known as polyphenols. Many of the therapeutic or health benefits of colored fruits and vegetables, cocoa, red wine, and green tea are directly related to their flavonoid content. The specially formulated flavonoids found in Theramine cannot be obtained from conventional foods in the necessary proportions to elicit a therapeutic response.
Other Ingredients
Theramine contains the following inactive or other ingredients, as fillers, excipients, and colorings: magnesium stearate, microcrystalline cellulose, Maltodextrin NF, gelatin (as the capsule material).
Physical Description
Theramine is a yellow to light brown powder. Theramine contains L-Glutamine, L-Arginine, L-Histidine, and L-Serine, 5-Hydroxytryptophan as Griffonia Seed Extract, GABA, Choline Bitartrate, Cinnamon, Cocoa, Hydrolyzed Whey Protein, and Grape Seed Extract.

CLINICAL PHARMACOLOGY
Mechanism of Action
Theramine acts by restoring and maintaining the balance of the neurotransmitters; GABA, nitric oxide, serotonin, and acetylcholine that are associated with pain disorders and inflammatory conditions. Theramine stimulates the production ACTH to reduce inflammation.
Metabolism
The amino acids in Theramine are primarily absorbed by the stomach and small intestines. All cells metabolize the amino acids in Theramine. Circulating tryptophan, arginine and choline blood levels determine the production of serotonin, nitric oxide, and acetylcholine.
Excretion
Theramine is not an inhibitor of cytochrome P450 1A2, 2C9, 2C19, 2D6, or 3A4. These isoenzymes are principally responsible for 95% of all detoxification of drugs, with CYP3A4 being responsible for detoxification of roughly 50% of drugs. Amino acids do not appear to have an effect on drug metabolizing enzymes.

INDICATIONS FOR USE
Theramine is intended for the clinical dietary management of the metabolic processes of pain disorders and inflammatory conditions.

CLINICAL EXPERIENCE
Administration of Theramine has demonstrated significant reduction in symptoms of pain and inflammation in patients with acute and chronic pain when used for the dietary management of the metabolic processes associated with pain disorders and inflammatory conditions. Administration of Theramine results in the induction and maintenance of pain relief in patients with pain disorders and inflammatory conditions.

PRECAUTIONS AND CONTRAINDICATIONS
Theramine is contraindicated in an extremely small number of patients with hypersensitivity to any of the nutritional components of Theramine.

ADVERSE REACTIONS
Oral supplementation with L-tryptophan, L-arginine or choline at high doses up to 15 grams daily is generally well tolerated. The most common adverse reactions of higher doses — from 15 to 30 grams daily — are nausea, abdominal cramps, and diarrhea. Some patients may experience these symptoms at lower doses. The total combined amount of amino acids in each Theramine capsule does not exceed 400 mg

DRUG INTERACTIONS
Theramine does not directly influence the pharmacokinetics of prescription drugs. Clinical experience has shown that administration of Theramine may allow for lowering the dose of co-administered drugs under physician supervision.

OVERDOSAGE

OVERDOSE
There is a negligible risk of overdose with Theramine as the total dosage of amino acids in a one month supply (90 capsules) is less than 36 grams. Overdose symptoms may include diarrhea, weakness, and nausea.
POST-MARKETING SURVEILLANCE
Post-marketing surveillance has shown no serious adverse reactions. Reported cases of mild rash and itching may have been associated with allergies to Theramine flavonoid ingredients, including cinnamon, cocoa, and chocolate. These reactions were transient in nature and subsided within 24 hours.

DOSAGE AND ADMINISTRATION
Recommended Administration For the dietary management of the metabolic processes associated with pain disorders and inflammatory conditions. Take (2) capsules one to three times daily or as directed by physician. As with most amino acid formulations Theramine should be taken without food to increase the absorption of key ingredients.

How Supplied
Theramine is supplied in purple and white, size 0 capsules in bottles of 60 or 90 capsules.
Physician Supervision
Theramine is a Medical Food product available by prescription only and must be used while the patient is under ongoing physician supervision.
U.S. patent pending.
Manufactured by Arizona Nutritional Supplements, Inc. Chandler AZ 85225
Distributed by Physician Therapeutics LLC, Los Angeles, CA 90077. www.ptlcentral.com
Copyright 2003-2006, Physician Therapeutics LLC, all rights reserved
NDC: 68405-1008-02
NDC: 68405-1008-03

Storage
Store at room temperature, 59-86OF (15-30OC) Protect from light and moisture. Theramine is supplied to physicians in a recyclable plastic bottle with a child-resistant cap.

PACKAGE LABEL

PHYSICIAN THERAPEUTICS THERAMINE Medical Food Rx only 90 Capsules Directions for use: Must be administered under medical supervision. For adults only. As a Medical Food, take one (1) or two (2) capsules every four hours or as directed by your medical practitioner. For the dietary management of Myalgia. Contains no added sugar, starch, wheat, yeast, preservatives, artificial flavor. Storage: Keep tightly closed in a cool dry place 8-320 C (45-900 F), relative humidity, below 50%. Warning: Keep this product out of the reach of children. NDC# 68405-1008-03 Ingredients: Each serving (per 2 capsules) contains: Proprietary Amino Acid Blend Griffonia Seed Extract (5-HTP), Whey Protein Hydrolysate, L-Arginini, L-Histidine (as L-Histidine HCl), L-Glutamine, L-Serine, Gamma Amino Butyric Acid, Choline Bitartrate, Cocoa (6% Theobromine) (fruit), Grape Extract (95% Polyphenols) (seed), Cinnamon (bark) Other Ingredients: Gelatin, Silicon Dioxide, Tricalcium phosphate, Vegetable Magnesium Stearate, Cellulose, FD and C Blue #1, FD and C red#3, titanium dioxide. Distributed by: Physician Therapeutics LLC, Los Angeles, CA 90077 www.ptlcentral.com Patent Pending

PACKAGE LABEL

A convenience Packed Medical Food and Drug
Prazolamine
Physician Therapeutics
Theramine 60 Capsules
Carisoprodol 350mg 30 Tablets
No Refills Without Physician Authorization
Rx Only
NDC # 68405-8028-06 of this co-pack
For the Dietary Management of Pain and Inflammation.
Two capsules twice daily or as directed byphysician. See product label and insert
Theramine
Medical Food
As prescribed by physician. See product label and product information insert.
Carisoprodol 350mg
Rx Drug
Physician Therapeutics LLC
Los Angeles, CA 90077
on November 21, 2006